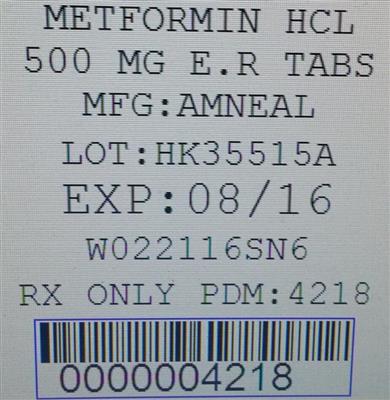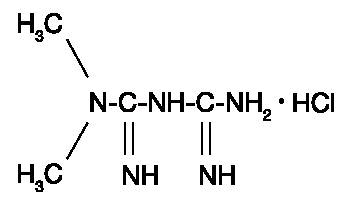 DRUG LABEL: Metformin Hydrochloride
NDC: 68151-4218 | Form: TABLET, EXTENDED RELEASE
Manufacturer: Carilion Materials Management
Category: prescription | Type: HUMAN PRESCRIPTION DRUG LABEL
Date: 20150921

ACTIVE INGREDIENTS: METFORMIN HYDROCHLORIDE 500 mg/1 1

METFORMIN HYDROCHLORIDE EXTENDED-RELEASE TABLETS, USP
Rx Only

DESCRIPTION

Metformin hydrochloride (HCl) extended-release tablets, USP are oral antihyperglycemic drugs used in the management of type 2 diabetes. Metformin HCl, USP (, -dimethylimidodicarbonimidic diamide hydrochloride) is not chemically or pharmacologically related to any other classes of oral antihyperglycemic agents. The structural formula is as shown: NN

Metformin HCl, USP is a white to off-white crystalline compound with a molecular formula of C H N • HCl and a molecular weight of 165.63. Metformin HCl, USP is freely soluble in water and is practically insoluble in acetone, ether, and chloroform. The pK of metformin is 12.4. The pH of a 1% aqueous solution of metformin HCl, USP is 6.68.4115a

Metformin HCl extended-release tablets, USP contain 500 mg or 750 mg of metformin HCl, USP as the active ingredient.

Metformin HCl extended-release tablets, USP 500 mg contain the inactive ingredients; colloidal silicon dioxide, hypromellose, magnesium stearate and microcrystalline cellulose.

Metformin HCl extended-release tablets, USP 750 mg contain the inactive ingredients; colloidal silicon dioxide, hypromellose and magnesium stearate.

Dissolution Method: Test 10

- Metformin HCl extended-release tablets, USP comprises a dual hydrophilic polymer matrix system. Metformin HCl, USP is combined with a drug release controlling polymer to form an "inner" phase, which is then incorporated as discrete particles into an "external" phase of a second polymer. After administration, fluid from the gastrointestinal (GI) tract enters the tablet, causing the polymers to hydrate and swell. Drug is released slowly from the dosage form by a process of diffusion through the gel matrix that is essentially independent of pH. The hydrated polymer system is not rigid and is expected to be broken up by normal peristalsis in the GI tract. The biologically inert components of the tablet may occasionally remain intact during GI transit and will be eliminated in the feces as a soft, hydrated mass. System Components and Performance

CLINICAL PHARMACOLOGY

Mechanism of Action

Metformin is an antihyperglycemic agent which improves glucose tolerance in patients with type 2 diabetes, lowering both basal and postprandial plasma glucose. Its pharmacologic mechanisms of action are different from other classes of oral antihyperglycemic agents. Metformin decreases hepatic glucose production, decreases intestinal absorption of glucose, and improves insulin sensitivity by increasing peripheral glucose uptake and utilization. Unlike sulfonylureas, metformin does not produce hypoglycemia in either patients with type 2 diabetes or normal subjects (except in special circumstances, see) and does not cause hyperinsulinemia. With metformin therapy, insulin secretion remains unchanged while fasting insulin levels and day-long plasma insulin response may actually decrease. PRECAUTIONS

Pharmacokinetics

Absorption and Bioavailability

Following a single oral dose of metformin HCl extended-release tablets, C is achieved with a median value of 7 hours and a range of 4 hours to 8 hours.max

At steady-state, the AUC and C are less than dose proportional for metformin HCl extended-release tablets within the range of 500 mg to 2000 mg administered once daily. Peak plasma levels are approximately 0.6, 1.1, 1.4, and 1.8 mcg/mL for 500, 1000, 1500, and 2000 mg once-daily doses, respectively. After repeated administration of metformin HCl extended-release tablets, metformin did not accumulate in plasma.max

Although the extent of metformin absorption (as measured by AUC) from the metformin HCl extended-release tablets increased by approximately 50% when given with food, there was no effect of food on C and T of metformin. Both high and low fat meals had the same effect on the pharmacokinetics of metformin HCl extended-release tablets.maxmax

Metabolism and Elimination

Intravenous single-dose studies in normal subjects demonstrate that metformin is excreted unchanged in the urine and does not undergo hepatic metabolism (no metabolites have been identified in humans) nor biliary excretion. Renal clearance is approximately 3.5 times greater than creatinine clearance, which indicates that tubular secretion is the major route of metformin elimination. Following oral administration, approximately 90% of the absorbed drug is eliminated via the renal route within the first 24 hours, with a plasma elimination half-life of approximately 6.2 hours. In blood, the elimination half-life is approximately 17.6 hours, suggesting that the erythrocyte mass may be a compartment of distribution.

Special Populations

Patients with Type 2 Diabetes

In the presence of normal renal function, there are no differences between single- or multiple-dose pharmacokinetics of metformin between patients with type 2 diabetes and normal subjects nor is there any accumulation of metformin in either group at usual clinical doses.

The pharmacokinetics of metformin HCl extended-release tablets in patients with type 2 diabetes are comparable to those in healthy normal adults.

Renal Insufficiency

In patients with decreased renal function (based on measured creatinine clearance), the plasma and blood half-life of metformin is prolonged and the renal clearance is decreased in proportion to the decrease in creatinine clearance (see). WARNINGS

Hepatic Insufficiency

No pharmacokinetic studies of metformin have been conducted in patients with hepatic insufficiency.

Geriatrics

Metformin HCl extended-release tablets treatment should not be initiated in patients ≥ 80 years of age unless measurement of creatinine clearance demonstrates that renal function is not reduced (see and). WARNINGSDOSAGE AND ADMINISTRATION

Gender

Metformin pharmacokinetic parameters did not differ significantly between normal subjects and patients with type 2 diabetes when analyzed according to gender (males = 19, females = 16).

Race

No studies of metformin pharmacokinetic parameters according to race have been performed.

Clinical Studies

Metformin HCl Extended-Release Tablets

A 24-week, double-blind, placebo-controlled study of metformin HCl extended-release tablets, taken once daily with the evening meal, was conducted in patients with type 2 diabetes who had failed to achieve glycemic control with diet and exercise (HbA 7% to 10%, FPG 126 to 270 mg/dL). Patients entering the study had a mean baseline HbA of 8% and a mean baseline FPG of 176 mg/dL. After 12 weeks treatment, mean HbA had increased from baseline by 0.1% and mean FPG decreased from baseline by 2 mg/dL in the placebo group, compared with a decrease in mean HbA of 0.6% and a decrease in mean FPG of 23 mg/dL in patients treated with metformin HCl extended-release tablets 1000 mg once daily.1c1c1c1c

Subsequently, the treatment dose was increased to 1500 mg once daily if HbA was ≥7% but <8% (patients with HbA ≥8% were discontinued from the study). At the final visit (24-week), mean HbA had increased 0.2% from baseline in placebo patients and decreased 0.6% with metformin HCl extended-release tablets.1c1c1c

A 16-week, double-blind, placebo-controlled, dose-response study of metformin HCl extended-release tablets, taken once daily with the evening meal or twice daily with meals, was conducted in patients with type 2 diabetes who had failed to achieve glycemic control with diet and exercise (HbA 7% to 11%, FPG 126 to 280 mg/dL). Changes in glycemic control and body weight are shown in .1c Table 1

Table 1: Summary of Mean Changes from Baseline in HbA , Fasting Plasma Glucose, and Body Weight at Final Visit (16-week study)*1c
 | Metformin HCl Extended-Release Tablets
 | 500 mg Once Daily | 1000 mg Once Daily | 1500 mg Once Daily | 2000 mg Once Daily | 1000 mg Twice Daily | Placebo
Hemoglobin A 1c (%) | (n=115) | (n=115) | (n=111) | (n=125) | (n=112) | (n=111)
Baseline | 8.2 | 8.4 | 8.3 | 8.4 | 8.4 | 8.4
Change at FINAL VISIT | -0.4 | -0.6 | -0.9 | -0.8 | -1.1 | 0.1
p-valuea | <0.001 | <0.001 | <0.001 | <0.001 | <0.001 | -
FPG (mg/dL) | (n=126) | (n=118) | (n=120) | (n=132) | (n=122) | (n=113)
Baseline | 182.7 | 183.7 | 178.9 | 181 | 181.6 | 179.6
Change at FINAL VISIT | -15.2 | -19.3 | -28.5 | -29.9 | -33.6 | 7.6
p-valuea | <0.001 | <0.001 | <0.001 | <0.001 | <0.001 | -
Body Weight (lbs) | (n=125) | (n=119) | (n=117) | (n=131) | (n=119) | (n=113)
Baseline | 192.9 | 191.8 | 188.3 | 195.4 | 192.5 | 194.3
Change at FINAL VISIT | -1.3 | -1.3 | -0.7 | -1.5 | -2.2 | -1.8
p-valuea | NS** | NS** | NS** | NS** | NS** | -

All patients on diet therapy at Baseline*

All comparisons versus Placeboa

Not statistically significant**

Compared with placebo, improvement in glycemic control was seen at all dose levels of metformin HCl extended-release tablets and treatment was not associated with any significant change in weight (see) for dosing recommendations for metformin HCl extended-release tablets. DOSAGE AND ADMINISTRATION

A 24-week, double-blind, randomized study of metformin HCl extended-release tablets, taken once daily with the evening meal, was conducted in patients with type 2 diabetes who had been treated with metformin HCl 500 mg twice daily for at least 8 weeks prior to study entry.

The metformin HCl dose had not necessarily been titrated to achieve a specific level of glycemic control prior to study entry. Patients qualified for the study if HbA was ≤8.5% and FPG was ≤200 mg/dL. Changes in glycemic control and body weight are shown in .1c Table 2

Table 2: Summary of Mean Changes from Baseline in HbA , Fasting Plasma Glucose, and Body Weight at Week 12 and at Final Visit (24-week study)*1c
 | Metformin HCl Extended-Release Tablets
 | 1000 mg Once Daily | 1500 mg Once Daily
Hemoglobin A 1c (%) | (n=72) | (n=66)
Baseline | 6.99 | 7.02
Change at 12 Weeks | 0.23 | 0.04
(95% CI) | (0.10, 0.36) | (-0.08, 0.15)
Change at FINAL VISIT | 0.27 | 0.13
(95 % CI) | (0.11, 0.43) | (-0.02, 0.28)
FPG (mg/dL) | (n=72) | (n=70)
Baseline | 131 | 131.4
Change at 12 Weeks | 9.5 | 3.7
(95% CI) | (4.4, 14.6) | (-0.4, 7.8)
Change at FINAL VISIT | 11.5 | 7.6
(95% CI) | (4.4, 18.6) | (1, 14.2)
Body Weight (lbs) | (n=74) | (n=71)
Baseline | 202.8 | 192.7
Change at 12 Weeks | 0.9 | 0.7
(95% CI) | (0, 2) | (-0.4, 1.8)
Change at FINAL VISIT | 1.1 | 0.9
(95 % CI) | (-0.2, 2.4) | (-0.4, 2)

After 12 weeks of treatment, there was an increase in mean HbA in all groups; in the metformin HCl extended-release tablets 1000 mg group, the increase from baseline of 0.23% was statistically significant (see).1c DOSAGE AND ADMINISTRATION

Changes in lipid parameters in the previously described placebo-controlled dose-response study of metformin HCl extended-release tablets are shown in . Table 3

Table 3: Summary of Mean Percent Changes from Baseline in Major Lipid Variables at Final Visit (16-week study)*
 | Metformin HCl Extended-Release Tablets
 | 500 mg Once Daily | 1000 mg Once Daily | 1500 mg Once Daily | 2000 mg Once Daily | 1000 mg Twice Daily | Placebo
Total Cholesterol (mg/dL) | (n=120) | (n=113) | (n=110) | (n=126) | (n=117) | (n=110)
Baseline | 210.3 | 218.1 | 214.6 | 204.4 | 208.2 | 208.6
Mean % Change at FINAL VISIT | 1% | 1.7% | 0.7% | -1.6% | -2.6% | 2.6%
Total Triglycerides (mg/dL) | (n=120) | (n=113) | (n=110) | (n=126) | (n=117) | (n=110)
Baseline | 220.2 | 211.9 | 198 | 194.2 | 179 | 211.7
Mean % Change at FINAL VISIT | 14.5% | 9.4% | 15.1% | 14.9% | 9.4% | 10.9%
LDL Cholesterol (mg/dL) | (n=119) | (n=113) | (n=109) | (n=126) | (n=117) | (n=107)
Baseline | 131 | 134.9 | 135.8 | 125.8 | 131.4 | 131.9
Mean % Change at FINAL VISIT | -1.4% | -1.6% | -3.5% | -3.3% | -5.5% | 3.2%
HDL Cholesterol (mg/dL) | (n=120) | (n=108) | (n=108) | (n=125) | (n=117) | (n=108)
Baseline | 40.8 | 41.6 | 40.6 | 40.2 | 42.4 | 39.4
Mean % Change at FINAL VISIT | 6.2% | 8.6% | 5.5% | 6.1% | 7.1% | 5.8%

All patients on diet therapy at Baseline *

Changes in lipid parameters in the previously described study of metformin HCl extended-release tablets are shown in . Table 4

Table 4: Summary of Mean Percent Changes from Baseline in Major Lipid Variables at Final Visit (24-week study)*
 | Metformin HCl Extended-Release Tablets
 | 1000 mg Once Daily | 1500 mg Once Daily
Total Cholesterol (mg/dL) | (n=70) | (n=66)
Baseline | 201.9 | 201.6
Mean % Change at FINAL VISIT | 1.3% | 0.1%
Total Triglycerides (mg/dL) | (n=70) | (n=66)
Baseline | 169.2 | 206.8
Mean % Change at FINAL VISIT | 25.3% | 33.4%
LDL Cholesterol (mg/dL) | (n=70) | (n=66)
Baseline | 126.2 | 115.7
Mean % Change at FINAL VISIT | -3.3% | -3.7%
HDL Cholesterol (mg/dL) | (n=70) | (n=65)
Baseline | 41.7 | 44.6
Mean % Change at FINAL VISIT | 1% | -2.1%

INDICATIONS AND USAGE

Metformin HCl extended-release tablets, USP are indicated as an adjunct to diet and exercise to improve glycemic control in patients with type 2 diabetes mellitus.

CONTRAINDICATIONS

Metformin HCl extended-release tablets, USP are contraindicated in patients with:

1. Renal disease or renal dysfunction (e.g., as suggested by serum creatinine levels ≥1.5 mg/dL [males], ≥1.4 mg/dL [females] or abnormal creatinine clearance) which may also result from conditions such as cardiovascular collapse (shock), acute myocardial infarction, and septicemia (see and).
WARNINGSPRECAUTIONS

2. Known hypersensitivity to metformin HCl, USP.

3. Acute or chronic metabolic acidosis, including diabetic ketoacidosis, without coma. Diabetic ketoacidosis should be treated with insulin.

Metformin HCl extended-release tablets, USP should be temporarily discontinued in patients undergoing radiologic studies involving intravascular administration of iodinated contrast materials, because use of such products may result in acute alteration of renal function. (See also .) PRECAUTIONS

WARNINGS

Lactic Acidosis: Lactic acidosis is a rare, but serious, metabolic complication that can occur due to metformin accumulation during treatment with metformin HCl extended-release tablets; when it occurs, it is fatal in approximately 50% of cases. Lactic acidosis may also occur in association with a number of pathophysiologic conditions, including diabetes mellitus, and whenever there is significant tissue hypoperfusion and hypoxemia. Lactic acidosis is characterized by elevated blood lactate levels (>5 mmol/L), decreased blood pH, electrolyte disturbances with an increased anion gap, and an increased lactate/pyruvate ratio. When metformin is implicated as the cause of lactic acidosis, metformin plasma levels >5 mcg/mL are generally found.

≥ The reported incidence of lactic acidosis in patients receiving metformin HCl is very low (approximately 0.03 cases/1000 patient-years, with approximately 0.015 fatal cases/1000 patient-years). In more than 20,000 patient-years exposure to metformin in clinical trials, there were no reports of lactic acidosis. Reported cases have occurred primarily in diabetic patients with significant renal insufficiency, including both intrinsic renal disease and renal hypoperfusion, often in the setting of multiple concomitant medical/surgical problems and multiple concomitant medications. Patients with congestive heart failure requiring pharmacologic management, in particular those with unstable or acute congestive heart failure who are at risk of hypoperfusion and hypoxemia, are at increased risk of lactic acidosis. The risk of lactic acidosis increases with the degree of renal dysfunction and the patient's age. The risk of lactic acidosis may, therefore, be significantly decreased by regular monitoring of renal function in patients taking metformin HCl extended-release tablets and by use of the minimum effective dose of metformin HCl extended-release tablets. In particular, treatment of the elderly should be accompanied by careful monitoring of renal function. Metformin HCl extended-release tablets treatment should not be initiated in patients 80 years of age unless measurement of creatinine clearance demonstrates that renal function is not reduced, as these patients are more susceptible to developing lactic acidosis. In addition, metformin HCl extended-release tablets should be promptly withheld in the presence of any condition associated with hypoxemia, dehydration, or sepsis. Because impaired hepatic function may significantly limit the ability to clear lactate, metformin HCl extended-release tablets should generally be avoided in patients with clinical or laboratory evidence of hepatic disease. Patients should be cautioned against excessive alcohol intake, either acute or chronic, when taking metformin HCl extended-release tablets, since alcohol potentiates the effects of metformin HCl on lactate metabolism. In addition, metformin HCl extended-release tablets should be temporarily discontinued prior to any intravascular radiocontrast study and for any surgical procedure (see also PRECAUTIONS).

The onset of lactic acidosis often is subtle, and accompanied only by nonspecific symptoms such as malaise, myalgias, respiratory distress, increasing somnolence, and nonspecific abdominal distress. There may be associated hypothermia, hypotension, and resistant bradyarrhythmias with more marked acidosis. The patient and the patient's physician must be aware of the possible importance of such symptoms and the patient should be instructed to notify the physician immediately if they occur (see also PRECAUTIONS). Metformin HCl extended-release tablets should be withdrawn until the situation is clarified. Serum electrolytes, ketones, blood glucose, and if indicated, blood pH, lactate levels, and even blood metformin levels may be useful. Once a patient is stabilized on any dose level of metformin HCl extended-release tablets, gastrointestinal symptoms, which are common during initiation of therapy, are unlikely to be drug related. Later occurrence of gastrointestinal symptoms could be due to lactic acidosis or other serious disease.

Levels of fasting venous plasma lactate above the upper limit of normal but less than 5 mmol/L in patients taking metformin HCl extended-release tablets do not necessarily indicate impending lactic acidosis and may be explainable by other mechanisms, such as poorly controlled diabetes or obesity, vigorous physical activity, or technical problems in sample handling. (See also PRECAUTIONS.)

Lactic acidosis should be suspected in any diabetic patient with metabolic acidosis lacking evidence of ketoacidosis (ketonuria and ketonemia).

Lactic acidosis is a medical emergency that must be treated in a hospital setting. In a patient with lactic acidosis who is taking metformin HCl extended-release tablets, the drug should be discontinued immediately and general supportive measures promptly instituted. Because metformin HCl is dialyzable (with a clearance of up to 170 mL/min under good hemodynamic conditions), prompt hemodialysis is recommended to correct the acidosis and remove the accumulated metformin. Such management often results in prompt reversal of symptoms and recovery. (See also CONTRAINDICATIONSand PRECAUTIONS.)

PRECAUTIONS

General

-There have been no clinical studies establishing conclusive evidence of macrovascular risk reduction with metformin HCl extended-release or any other anti-diabetic drug Macrovascular Outcomes.

-Metformin is known to be substantially excreted by the kidney, and the risk of metformin accumulation and lactic acidosis increases with the degree of impairment of renal function. Thus, patients with serum creatinine levels above the upper limit of normal for their age should not receive metformin HCl extended-release tablets. In patients with advanced age, metformin HCl extended-release tablets should be carefully titrated to establish the minimum dose for adequate glycemic effect, because aging is associated with reduced renal function. In elderly patients, particularly those ≥80 years of age, renal function should be monitored regularly and, generally, metformin HCl extended-release tablets should not be titrated to the maximum dose (see and). Monitoring of renal function WARNINGSDOSAGE AND ADMINISTRATION

Before initiation of metformin HCl extended-release tablets therapy and at least annually thereafter, renal function should be assessed and verified as normal. In patients in whom development of renal dysfunction is anticipated, renal function should be assessed more frequently and metformin HCl extended-release tablets discontinued if evidence of renal impairment is present.

-Concomitant medication(s) that may affect renal function or result in significant hemodynamic change or may interfere with the disposition of metformin, such as cationic drugs that are eliminated by renal tubular secretion (see), should be used with caution. Use of concomitant medications that may affect renal function or metformin disposition PRECAUTIONS: Drug Interactions

-Intravascular contrast studies with iodinated materials can lead to acute alteration of renal function and have been associated with lactic acidosis in patients receiving metformin (see). Therefore, in patients in whom any such study is planned, metformin HCl extended-release tablets should be temporarily discontinued at the time of or prior to the procedure, and withheld for 48 hours subsequent to the procedure and reinstituted only after renal function has been re-evaluated and found to be normal. Radiologic studies involving the use of intravascular iodinated contrast materials (for example, intravenous urogram, intravenous cholangiography, angiography, and computed tomography (CT) scans with intravascular contrast materials) CONTRAINDICATIONS

-Cardiovascular collapse (shock) from whatever cause, acute congestive heart failure, acute myocardial infarction and other conditions characterized by hypoxemia have been associated with lactic acidosis and may also cause prerenal azotemia. When such events occur in patients on metformin HCl extended-release tablets therapy, the drug should be promptly discontinued. Hypoxic states

- Metformin HCl extended-release tablets therapy should be temporarily suspended for any surgical procedure (except minor procedures not associated with restricted intake of food and fluids) and should not be restarted until the patient's oral intake has resumed and renal function has been evaluated as normal. Surgical procedures

-Alcohol is known to potentiate the effect of metformin on lactate metabolism. Patients, therefore, should be warned against excessive alcohol intake, acute or chronic, while receiving metformin HCl extended-release tablets. Alcohol intake

-Since impaired hepatic function has been associated with some cases of lactic acidosis, metformin HCl extended-release tablets should generally be avoided in patients with clinical or laboratory evidence of hepatic disease. Impaired hepatic function

-Measurement of hematologic parameters on an annual basis is advised in patients on metformin HCl extended-release tablets and any apparent abnormalities should be appropriately investigated and managed (see). Vitamin B 12 levels PRECAUTIONS: Laboratory Tests

Certain individuals (those with inadequate Vitamin B or calcium intake or absorption) appear to be predisposed to developing subnormal Vitamin B levels. In these patients, routine serum Vitamin B measurements at two- to three-year intervals may be useful.121212

-A patient with type 2 diabetes previously well controlled on metformin HCl extended-release tablets who develops laboratory abnormalities or clinical illness (especially vague and poorly defined illness) should be evaluated promptly for evidence of ketoacidosis or lactic acidosis. Evaluation should include serum electrolytes and ketones, blood glucose and, if indicated, blood pH, lactate, pyruvate, and metformin levels. If acidosis of either form occurs, metformin HCl extended-release tablets must be stopped immediately and other appropriate corrective measures initiated (see also). Change in clinical status of patients with previously controlled type 2 diabetes WARNINGS

-Hypoglycemia does not occur in patients receiving metformin HCl extended-release tablets alone under usual circumstances of use, but could occur when caloric intake is deficient, when strenuous exercise is not compensated by caloric supplementation, or during concomitant use with other glucose-lowering agents (such as sulfonylureas and insulin) or ethanol. Hypoglycemia

Elderly, debilitated, or malnourished patients, and those with adrenal or pituitary insufficiency or alcohol intoxication are particularly susceptible to hypoglycemic effects. Hypoglycemia may be difficult to recognize in the elderly, and in people who are taking beta-adrenergic blocking drugs.

-When a patient stabilized on any diabetic regimen is exposed to stress such as fever, trauma, infection, or surgery, a temporary loss of glycemic control may occur. At such times, it may be necessary to withhold metformin HCl extended-release tablets and temporarily administer insulin. Metformin HCl extended-release tablets may be reinstituted after the acute episode is resolved. Loss of control of blood glucose

The effectiveness of oral antidiabetic drugs in lowering blood glucose to a targeted level decreases in many patients over a period of time. This phenomenon, which may be due to progression of the underlying disease or to diminished responsiveness to the drug, is known as secondary failure, to distinguish it from primary failure in which the drug is ineffective during initial therapy. Should secondary failure occur with either metformin HCl extended-release tablets or sulfonylurea monotherapy, combined therapy with metformin HCl extended-release tablets and sulfonylurea may result in a response. Should secondary failure occur with combined metformin HCl extended-release tablets /sulfonylurea therapy, it may be necessary to consider therapeutic alternatives including initiation of insulin therapy.

Information for Patients

Patients should be informed of the potential risks and benefits of metformin HCl extended-release tablets and of alternative modes of therapy. They should also be informed about the importance of adherence to dietary instructions, of a regular exercise program, and of regular testing of blood glucose, glycosylated hemoglobin, renal function, and hematologic parameters.

The risks of lactic acidosis, its symptoms, and conditions that predispose to its development, as noted in the and sections, should be explained to patients. Patients should be advised to discontinue metformin HCl extended-release tablets immediately and to promptly notify their health practitioner if unexplained hyperventilation, myalgia, malaise, unusual somnolence, or other nonspecific symptoms occur. Once a patient is stabilized on any dose level of metformin HCl extended-release tablets, gastrointestinal symptoms, which are common during initiation of metformin therapy, are unlikely to be drug related. Later occurrence of gastrointestinal symptoms could be due to lactic acidosis or other serious disease. WARNINGSPRECAUTIONS

Patients should be counseled against excessive alcohol intake, either acute or chronic, while receiving metformin HCl extended-release tablets.

Metformin HCl extended-release tablets alone do not usually cause hypoglycemia, although it may occur when metformin HCl extended-release tablets are used in conjunction with oral sulfonylureas and insulin. When initiating combination therapy, the risks of hypoglycemia, its symptoms and treatment, and conditions that predispose to its development should be explained to patients and responsible family members. (See printed below.) Patient Information

Patients should be informed that metformin HCl extended-release tablets must be swallowed whole and not crushed or chewed, and that the inactive ingredients may occasionally be eliminated in the feces as a soft mass that may resemble the original tablet.

Laboratory Tests

Response to all diabetic therapies should be monitored by periodic measurements of fasting blood glucose and glycosylated hemoglobin levels, with a goal of decreasing these levels toward the normal range. During initial dose titration, fasting glucose can be used to determine the therapeutic response. Thereafter, both glucose and glycosylated hemoglobin should be monitored. Measurements of glycosylated hemoglobin may be especially useful for evaluating long-term control (see also). DOSAGE AND ADMINISTRATION

Initial and periodic monitoring of hematologic parameters (e.g., hemoglobin/hematocrit and red blood cell indices) and renal function (serum creatinine) should be performed, at least on an annual basis.

Drug Interactions (Clinical Evaluation of Drug Interactions Conducted with Metformin HCl)

-In a single-dose interaction study in type 2 diabetes patients, co-administration of metformin and glyburide did not result in any changes in either metformin pharmacokinetics or pharmacodynamics. Decreases in glyburide AUC and C were observed, but were highly variable. Glyburidemax

The single-dose nature of this study and the lack of correlation between glyburide blood levels and pharmacodynamic effects, makes the clinical significance of this interaction uncertain (see). DOSAGE AND ADMINISTRATION: Concomitant Metformin HCl Extended-Release Tablets and Oral Sulfonylurea Therapy in Adult Patients

-A single-dose, metformin-furosemide drug interaction study in healthy subjects demonstrated that pharmacokinetic parameters of both compounds were affected by co-administration. Furosemide increased the metformin plasma and blood C by 22% and blood AUC by 15%, without any significant change in metformin renal clearance. When administered with metformin, the C and AUC of furosemide were 31% and 12% smaller, respectively, than when administered alone, and the terminal half-life was decreased by 32%, without any significant change in furosemide renal clearance. No information is available about the interaction of metformin and furosemide when co-administered chronically. Furosemidemaxmax

-A single-dose, metformin-nifedipine drug interaction study in normal healthy volunteers demonstrated that co-administration of nifedipine increased plasma metformin C and AUC by 20% and 9%, respectively, and increased the amount excreted in the urine. T and half-life were unaffected. Nifedipine appears to enhance the absorption of metformin. Metformin had minimal effects on nifedipine. Nifedipinemaxmax

-Cationic drugs (e.g., amiloride, digoxin, morphine, procainamide, quinidine, quinine, ranitidine, triamterene, trimethoprim, or vancomycin) that are eliminated by renal tubular secretion theoretically have the potential for interaction with metformin by competing for common renal tubular transport systems. Such interaction between metformin and oral cimetidine has been observed in normal healthy volunteers in both single- and multiple-dose, metformin-cimetidine drug interaction studies, with a 60% increase in peak metformin plasma and whole blood concentrations and a 40% increase in plasma and whole blood metformin AUC. There was no change in elimination half-life in the single-dose study. Metformin had no effect on cimetidine pharmacokinetics. Although such interactions remain theoretical (except for cimetidine), careful patient monitoring and dose adjustment of metformin HCl extended-release tablets and/or the interfering drug is recommended in patients who are taking cationic medications that are excreted via the proximal renal tubular secretory system. Cationic drugs

-Certain drugs tend to produce hyperglycemia and may lead to loss of glycemic control. These drugs include the thiazides and other diuretics, corticosteroids, phenothiazines, thyroid products, estrogens, oral contraceptives, phenytoin, nicotinic acid, sympathomimetics, calcium channel blocking drugs, and isoniazid. When such drugs are administered to a patient receiving metformin HCl extended-release tablets, the patient should be closely observed for loss of blood glucose control. When such drugs are withdrawn from a patient receiving metformin HCl extended-release tablets, the patient should be observed closely for hypoglycemia. Other

In healthy volunteers, the pharmacokinetics of metformin and propranolol, and metformin and ibuprofen were not affected when coadministered in single-dose interaction studies.

Metformin is negligibly bound to plasma proteins and is, therefore, less likely to interact with highly protein-bound drugs such as salicylates, sulfonamides, chloramphenicol, and probenecid, as compared to the sulfonylureas, which are extensively bound to serum proteins.

Carcinogenesis, Mutagenesis, Impairment of Fertility

Long-term carcinogenicity studies have been performed in rats (dosing duration of 104 weeks) and mice (dosing duration of 91 weeks) at doses up to and including 900 mg/kg/day and 1500 mg/kg/day, respectively. These doses are both approximately four times the maximum recommended human daily dose of 2000 mg based on body surface area comparisons. No evidence of carcinogenicity with metformin was found in either male or female mice. Similarly, there was no tumorigenic potential observed with metformin in male rats. There was, however, an increased incidence of benign stromal uterine polyps in female rats treated with 900 mg/kg/day.

There was no evidence of a mutagenic potential of metformin in the following tests: Ames test (), gene mutation test (mouse lymphoma cells), or chromosomal aberrations test (human lymphocytes). Results in the mouse micronucleus test were also negative. in vitro S. typhimuriumin vivo

Fertility of male or female rats was unaffected by metformin when administered at doses as high as 600 mg/kg/day, which is approximately three times the maximum recommended human daily dose based on body surface area comparisons.

Pregnancy

Teratogenic Effects: Pregnancy Category B

Recent information strongly suggests that abnormal blood glucose levels during pregnancy are associated with a higher incidence of congenital abnormalities. Most experts recommend that insulin be used during pregnancy to maintain blood glucose levels as close to normal as possible. Because animal reproduction studies are not always predictive of human response, metformin HCl extended-release tablets should not be used during pregnancy unless clearly needed.

There are no adequate and well-controlled studies in pregnant women with metformin HCl extended-release tablets. Metformin was not teratogenic in rats and rabbits at doses up to 600 mg/kg/day. This represents an exposure of about two and six times the maximum recommended human daily dose of 2000 mg based on body surface area comparisons for rats and rabbits, respectively. Determination of fetal concentrations demonstrated a partial placental barrier to metformin.

Nursing Mothers

Studies in lactating rats show that metformin is excreted into milk and reaches levels comparable to those in plasma. Similar studies have not been conducted in nursing mothers. Because the potential for hypoglycemia in nursing infants may exist, a decision should be made whether to discontinue nursing or to discontinue the drug, taking into account the importance of the drug to the mother. If metformin HCl extended-release tablets are discontinued, and if diet alone is inadequate for controlling blood glucose, insulin therapy should be considered.

Pediatric Use

Safety and effectiveness of metformin HCl extended-release tablets in pediatric patients have not been established.

Geriatric Use

Controlled clinical studies of metformin HCl extended-release tablets did not include sufficient numbers of elderly patients to determine whether they respond differently from younger patients, although other reported clinical experience has not identified differences in responses between the elderly and younger patients. Metformin is known to be substantially excreted by the kidney and because the risk of serious adverse reactions to the drug is greater in patients with impaired renal function, metformin HCl extended-release tablets should only be used in patients with normal renal function (see , , and). Because aging is associated with reduced renal function, metformin HCl extended-release tablets should be used with caution as age increases. Care should be taken in dose selection and should be based on careful and regular monitoring of renal function. Generally, elderly patients should not be titrated to the maximum dose of metformin HCl extended-release tablets (see also and). CONTRAINDICATIONSWARNINGSCLINICAL PHARMACOLOGY: Pharmacokinetics WARNINGSDOSAGE AND ADMINISTRATION

ADVERSE REACTIONS

In worldwide clinical trials over 900 patients with type 2 diabetes have been treated with metformin HCl extended-release tablets in placebo- and active-controlled studies. In placebo-controlled trials, 781 patients were administered metformin HCl extended-release tablets and 195 patients received placebo. Adverse reactions reported in greater than 5% of the metformin HCl extended-release tablets patients, and that were more common in metformin HCl extended-release tablets - than placebo-treated patients, are listed in . Table 5

Table 5: Most Common Adverse Reactions (> 5 Percent) in Placebo-Controlled Studies of Metformin HCl Extended-Release Tablets*
 | Metformin HCl Extended-Release Tablets N=781 | Placebo N=195
Adverse Reactions | % of Patients
Diarrhea | 9.6 | 2.6
Nausea / Vomiting | 6.5 | 1.5

Reactions that were more common in metformin HCl extended-release tablets-than placebo-treated patients.*

Diarrhea led to discontinuation of study medication in 0.6% of patients treated with metformin HCl extended-release tablets. Additionally, the following adverse reactions were reported in ≥1% to ≤5% of metformin HCl extended-release tablets patients and were more commonly reported with metformin HCl extended-release tablets than placebo: abdominal pain, constipation, distention abdomen, dyspepsia/heartburn, flatulence, dizziness, headache, upper respiratory infection, taste disturbance.

OVERDOSAGE

Overdose of metformin HCl has occurred, including ingestion of amounts greater than 50 grams. Hypoglycemia was reported in approximately 10% of cases, but no causal association with metformin HCl has been established. Lactic acidosis has been reported in approximately 32% of metformin overdose cases (see). Metformin is dialyzable with a clearance of up to 170 mL/min under good hemodynamic conditions. Therefore, hemodialysis may be useful for removal of accumulated drug from patients in whom metformin overdosage is suspected. WARNINGS

DOSAGE AND ADMINISTRATION

There is no fixed dosage regimen for the management of hyperglycemia in patients with type 2 diabetes with metformin HCl extended-release tablets, USP or any other pharmacologic agent. Dosage of metformin HCl extended-release tablets, USP must be individualized on the basis of both effectiveness and tolerance, while not exceeding the maximum recommended daily doses. The maximum recommended daily dose of metformin HCl extended-release tablets, USP in adults is 2000 mg.

Metformin HCl extended-release tablets, USP should generally be given once daily with the evening meal. Metformin HCl extended-release tablets, USP should be started at a low dose, with gradual dose escalation, both to reduce gastrointestinal side effects and to permit identification of the minimum dose required for adequate glycemic control of the patient.

During treatment initiation and dose titration (see), fasting plasma glucose should be used to determine the therapeutic response to metformin HCl extended-release tablets, USP and identify the minimum effective dose for the patient. Thereafter, glycosylated hemoglobin should be measured at intervals of approximately three months. Monitoring of blood glucose and glycosylated hemoglobin will also permit detection of primary failure, i.e., inadequate lowering of blood glucose at the maximum recommended dose of medication, and secondary failure, i.e., loss of an adequate blood glucose lowering response after an initial period of effectiveness. Recommended Dosing Schedule The therapeutic goal should be to decrease both fasting plasma glucose and glycosylated hemoglobin levels to normal or near normal by using the lowest effective dose of metformin HCl extended-release tablets, USP, either when used as monotherapy or in combination with sulfonylurea or insulin.

Short-term administration of metformin HCl extended-release tablets, USP may be sufficient during periods of transient loss of control in patients usually well-controlled on diet alone.

Occasionally, the inactive ingredients of metformin HCl extended-release tablets, USP will be eliminated in the feces as a soft, hydrated mass. (See printed below.) Metformin HClextended-release tablets, USP must be swallowed whole and never crushed or chewed. Patient Information

Recommended Dosing Schedule

- In general, clinically significant responses are not seen at doses below 1500 mg per day. However, a lower recommended starting dose and gradually increased dosage is advised to minimize gastrointestinal symptoms. Adults

The usual starting dose of metformin HCl extended-release tablets, USP is 500 mg once daily with the evening meal. Dosage increases should be made in increments of 500 mg weekly, up to a maximum of 2000 mg once daily with the evening meal. If glycemic control is not achieved on metformin HCl extended-release tablets, USP 2000 mg once daily, a trial of metformin HCl extended-release tablets, USP 1000 mg twice daily should be considered. (See) CLINICAL PHARMACOLOGY, Clinical Studies.

- Safety and effectiveness of metformin HCl extended-release tablets, USP in pediatric patients have not been established. Pediatrics

Transfer From Other Antidiabetic Therapy

When transferring patients from standard oral hypoglycemic agents other than chlorpropamide to metformin HCl extended-release tablets, USP, no transition period generally is necessary. When transferring patients from chlorpropamide, care should be exercised during the first two weeks because of the prolonged retention of chlorpropamide in the body, leading to overlapping drug effects and possible hypoglycemia.

Concomitant Metformin HCl Extended-Release Tablets, USP and Oral Sulfonylurea Therapy in Adult Patients

If patients have not responded to four weeks of the maximum dose of metformin HCl extended-release tablets, USP monotherapy, consideration should be given to gradual addition of an oral sulfonylurea while continuing metformin HCl extended-release tablets, USP at the maximum dose, even if prior primary or secondary failure to a sulfonylurea has occurred. Clinical and pharmacokinetic drug-drug interaction data are currently available only for metformin plus glyburide (glibenclamide).

With concomitant metformin HCl extended-release tablets, USP and sulfonylurea therapy, the desired control of blood glucose may be obtained by adjusting the dose of each drug. With concomitant metformin HCl extended-release tablets, USP and sulfonylurea therapy, the risk of hypoglycemia associated with sulfonylurea therapy continues and may be increased. Appropriate precautions should be taken. (See Package Insert of the respective sulfonylurea.)

If patients have not satisfactorily responded to one to three months of concomitant therapy with the maximum dose of metformin HCl extended-release tablets, USP and the maximum dose of an oral sulfonylurea, consider therapeutic alternatives including switching to insulin with or without metformin HCl extended-release tablets, USP.

Concomitant Metformin HCl Extended-Release Tablets, USP and Insulin Therapy in Adult Patients

The current insulin dose should be continued upon initiation of metformin HCl extended-release tablets, USP therapy. Metformin HCl extended-release tablets, USP therapy should be initiated at 500 mg once daily in patients on insulin therapy. For patients not responding adequately, the dose of metformin HCl extended-release tablets, USP should be increased by 500 mg after approximately 1 week and by 500 mg every week thereafter until adequate glycemic control is achieved. The maximum recommended daily dose is 2000 mg for metformin HCl extended-release tablets, USP. It is recommended that the insulin dose be decreased by 10% to 25% when fasting plasma glucose concentrations decrease to less than 120 mg/dL in patients receiving concomitant insulin and metformin HCl extended-release tablets, USP. Further adjustment should be individualized based on glucose-lowering response.

Specific Patient Populations

Metformin HCl extended-release tablets, USP are not recommended for use in pregnancy. Metformin HCl extended-release tablets, USP are not recommended in pediatric patients (below the age of 17 years).

The initial and maintenance dosing of metformin HCl extended-release tablets, USP should be conservative in patients with advanced age, due to the potential for decreased renal function in this population. Any dosage adjustment should be based on a careful assessment of renal function. Generally, elderly, debilitated, and malnourished patients should not be titrated to the maximum dose of metformin HCl extended-release tablets, USP.

Monitoring of renal function is necessary to aid in prevention of lactic acidosis, particularly in the elderly. (See) WARNINGS.

HOW SUPPLIED

NDC:68151-4218-7 1 TABLET, EXTENDED RELEASES in a CUP, UNIT-DOSE

Patient Information

Metformin Hydrochloride Extended-Release Tablets

Read this information carefully before you start taking this medicine and each time you refill your prescription. There may be new information. This information does not take the place of your doctor's advice. Ask your doctor or pharmacist if you do not understand some of this information or if you want to know more about this medicine.

What is Metformin HCl?

Metformin HCl is used to treat type 2 diabetes. This is also known as noninsulin-dependent diabetes mellitus. People with type 2 diabetes are not able to make enough insulin or respond normally to the insulin their bodies make. When this happens, sugar (glucose) builds up in the blood. This can lead to serious medical problems including kidney damage, amputations, and blindness. Diabetes is also closely linked to heart disease. The main goal of treating diabetes is to lower your blood sugar to a normal level.

High blood sugar can be lowered by diet and exercise, by a number of medicines taken by mouth, and by insulin shots. Before you take metformin HCl, try to control your diabetes by exercise and weight loss. While you take your diabetes medicine, continue to exercise and follow the diet advised for your diabetes. No matter what your recommended diabetes management plan is, studies have shown that maintaining good blood sugar control can prevent or delay complications of diabetes, such as blindness.

Metformin HCl extended-release tablets work longer in your body. Metformin HCl helps control your blood sugar in a number of ways. These include helping your body respond better to the insulin it makes naturally, decreasing the amount of sugar your liver makes, and decreasing the amount of sugar your intestines absorb. Metformin HCl does not cause your body to make more insulin. Because of this, when taken alone, they rarely cause hypoglycemia (low blood sugar), and usually do not cause weight gain. However, when they are taken with a sulfonylurea or with insulin, hypoglycemia is more likely to occur, as is weight gain.

WARNING: A small number of people who have taken metformin HCl have developed a serious condition called lactic acidosis. Lactic acidosis is caused by a buildup of lactic acid in the blood. This happens more often in people with kidney problems. Most people with kidney problems should not take metformin HCl. (See "What are the side effects of metformin HCl?")

Who should not take Metformin HCl?

Some conditions increase your chance of getting lactic acidosis, or cause other problems if you take either of these medicines. Most of the conditions listed below can increase your chance of getting lactic acidosis.

Do not take Metformin HCl if you:

- have kidney problems
- have liver problems
- have heart failure that is treated with medicines, such as Lanoxin® (digoxin) or Lasix® (furosemide)
- drink a lot of alcohol. This means you binge drink for short periods or drink all the time
- are seriously dehydrated (have lost a lot of water from your body)
- are going to have an x-ray procedure with injection of dyes (contrast agents)
- are going to have surgery
- develop a serious condition, such as heart attack, severe infection, or a stroke
- are 80 years or older and you have NOT had your kidney function tested

Tell your doctor if you are pregnant or plan to become pregnant. Metformin HCl may not be right for you. Talk with your doctor about your choices. You should also discuss your choices with your doctor if you are nursing a child.

Can Metformin HCl Extended-Release Tablets be used in children?

Metformin HCl extended-release tablets have not been studied in children.

How should I take Metformin HCl?

Your doctor will tell you how much medicine to take and when to take it. You will probably start out with a low dose of the medicine. Your doctor may slowly increase your dose until your blood sugar is better controlled. You should take metformin HCl with meals.

Your doctor may have you take other medicines along with metformin HCl to control your blood sugar. These medicines may include insulin shots. Taking metformin HCl with insulin may help you better control your blood sugar while reducing the insulin dose.

Continue your exercise and diet program and test your blood sugar regularly while taking metformin HCl. Your doctor will monitor your diabetes and may perform blood tests on you from time to time to make sure your kidneys and your liver are functioning normally. There is no evidence that metformin HCl causes harm to the liver or kidneys.

Tell your doctor if you:

- have an illness that causes severe vomiting, diarrhea or fever, or if you drink a much lower amount of liquid than normal. These conditions can lead to severe dehydration (loss of water in your body). You may need to stop taking metformin HCl for a short time.
- plan to have surgery or an x-ray procedure with injection of dye (contrast agent). You may need to stop taking metformin HCl extended-release tablets for a short time.
- start to take other medicines or change how you take a medicine. Metformin HCl can affect how well other drugs work, and some drugs can affect how well metformin HCl works. Some medicines may cause high blood sugar.

Occasionally, the inactive ingredients of metformin HCl extended-release tablets may be eliminated as a soft mass in your stool that may look like the original tablet; this is not harmful and will not affect the way metformin HCl extended-release tablets works to control your diabetes. Metformin HCl extended-release tablets must be swallowed whole and never crushed or chewed.

What should I avoid while taking Metformin HCl?

Do not drink a lot of alcoholic drinks while taking metformin HCl. This means you should not binge drink for short periods, and you should not drink a lot of alcohol on a regular basis.

Alcohol can increase the chance of getting lactic acidosis.

What are the side effects of Metformin HCl?

Lactic acidosis caused by metformin HCl is rare and has occurred mostly in people whose kidneys were not working normally. Although rare, if lactic acidosis does occur, it can be fatal in up to half the people who develop it. Lactic Acidosis. In rare cases, metformin HClcan cause a serious side effect called lactic acidosis. This is caused by a buildup of lactic acid in your blood. This build-up can cause serious damage.

It is also important for your liver to be working normally when you take metformin HCl. Your liver helps remove lactic acid from your blood.

Make sure you tell your doctor before you use metformin HCl if you have kidney or liver problems. You should also stop using metformin HCl and call your doctor right away if you have signs of lactic acidosis. Lactic acidosis is a medical emergency that must be treated in a hospital.

Signs of lactic acidosis are:

- feeling very weak, tired, or uncomfortable
- unusual muscle pain
- trouble breathing
- unusual or unexpected stomach discomfort
- feeling cold
- feeling dizzy or lightheaded
- suddenly developing a slow or irregular heartbeat

If your medical condition suddenly changes, stop taking metformin HCl and call your doctor right away. This may be a sign of lactic acidosis or another serious side effect.

Other Side Effects.

Common side effects of metformin HCl include diarrhea, nausea, and upset stomach. These side effects generally go away after you take the medicine for a while. Taking your medicine with meals can help reduce these side effects. Tell your doctor if the side effects bother you a lot, last for more than a few weeks, come back after they've gone away, or start later in therapy. You may need a lower dose or need to stop taking the medicine for a short period or for good.

About 3 out of every 100 people who take metformin HCl have an unpleasant metallic taste when they start taking the medicine. It lasts for a short time.

Metformin HCl rarely cause hypoglycemia (low blood sugar) by themselves. However, hypoglycemia can happen if you do not eat enough, if you drink alcohol, or if you take other medicines to lower blood sugar.

General advice about prescription medicines

If you have questions or problems, talk with your doctor or other healthcare provider. You can ask your doctor or pharmacist for the information about metformin HCl that is written for health care professionals. Medicines are sometimes prescribed for purposes other than those listed in a patient information leaflet. Do not use metformin HCl for a condition for which it was not prescribed. Do not share your medicine with other people.

Questions or comments?

Call 1-877-835-5472 Monday through Friday 9AM to 5PM EST.

Distributed by: Bridgewater, NJ 08807
Amneal Pharmaceuticals

Rev. 09-2015-01